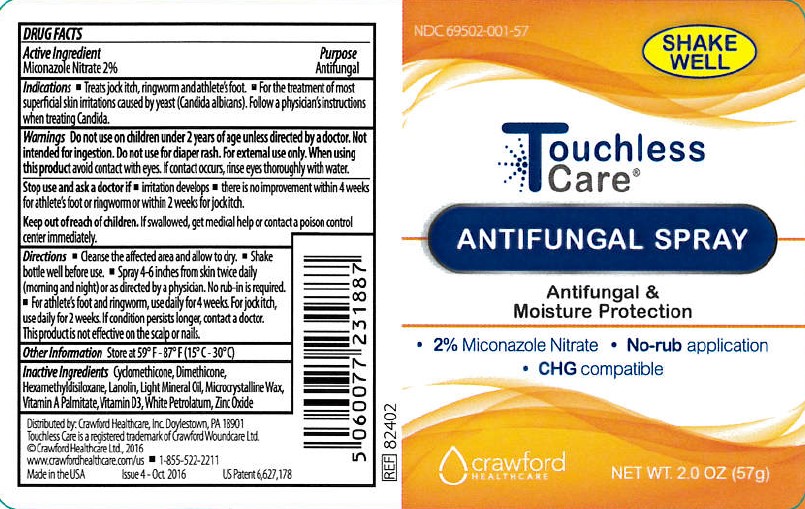 DRUG LABEL: Touchless Care ANTIFUNGAL
NDC: 69502-001 | Form: SPRAY
Manufacturer: Crawford Healthcare, Inc.
Category: otc | Type: HUMAN OTC DRUG LABEL
Date: 20170216

ACTIVE INGREDIENTS: MICONAZOLE NITRATE 2 g/100 g
INACTIVE INGREDIENTS: LANOLIN; VITAMIN A PALMITATE; MINERAL OIL; DIMETHICONE; CYCLOMETHICONE; PETROLATUM; ZINC OXIDE; HEXAMETHYLDISILOXANE; CHOLECALCIFEROL; MICROCRYSTALLINE WAX

Touchless Care ANTIFUNGAL SPRAY

Active Ingredient

Miconazole Nitrate 2%

Purpose

Antifungal

Indications

- Treats jock itch, ringworm and athlete's foot
- For the treatment of most superficial skin irritations caused by yeast (Candida albicans). Follow a physician's instructions when treating Candida.

Warnings

Do not use on children under 2 years of age unless directed by a doctor. Not intended for ingestion. Do not use for diaper rash. For external use only. When using this product avoid contact with eyes. If contact occurs, rinse eyes thoroughly with water.

Stop use and ask a doctor if

- irritation develops
- there is no improvement within 4 weeks for athlete's foot or ringworm or within 2 weeks for jock itch.

Keep out of reach of children.

If swallowed, get medical help or contact a poison control center immediately.

Directions

- Cleanse the affected area and allow to dry.
- Shake bottle well before use.
- Spray 4-6 inches from skin twice daily (morning and night) or as directed by a physician. No rub-in is required.
- For athlete's foot and ringworm, use daily for 4 weeks. For jock itch, use daily for 2 weeks. If condition persists longer, contact a doctor. This product is not effective on the scalp or nails.

Other Information

Store at 59oF - 87oF (15oC - 30oC)

Inactive Ingredients

Cyclomethicone, Dimethicone, Hexamethyldisiloxane, Lanolin, Light Mineral Oil, Microcrystalline Wax, Vitamin A Palmitate, Vitamin D3, White Petrolatum, Zinc Oxide

SPL Unclassified Section

Distributed by: Crawford Healthcare, Inc. Doylestown, PA 18901

Touchless Care is a registered trademark of Crawford Woundcare Ltd.

© Crawford Healthcare Ltd., 2016

www.crawfordhealthcare.com/us

1-855-522-2211

Made in the USA

Package Label

Antifungal label